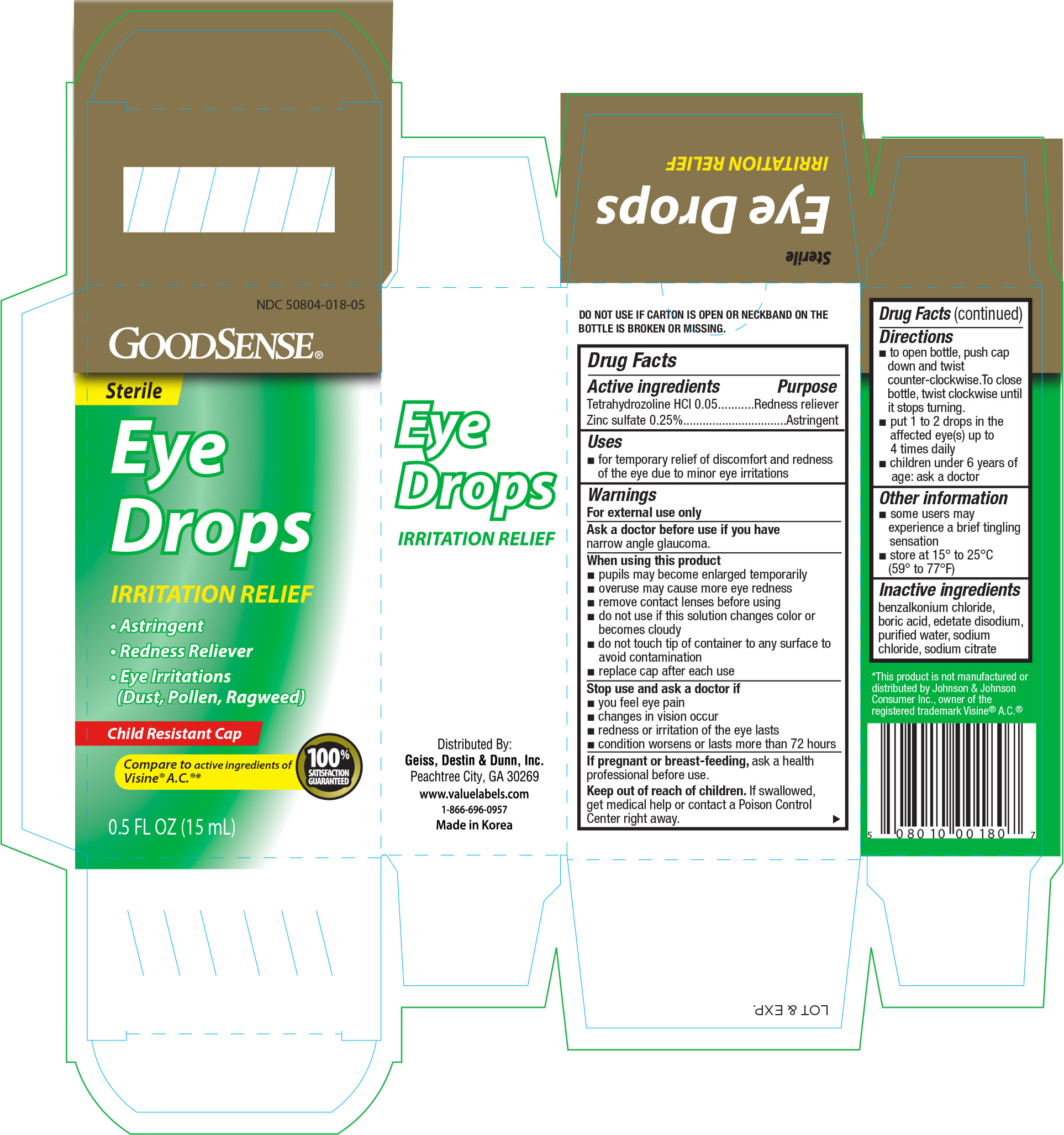 DRUG LABEL: GoodSense Irritation Relief Eye
NDC: 50804-018 | Form: SOLUTION/ DROPS
Manufacturer: Geiss, Destin & Dunn, Inc.
Category: otc | Type: HUMAN OTC DRUG LABEL
Date: 20160324

ACTIVE INGREDIENTS: TETRAHYDROZOLINE HYDROCHLORIDE .05 mg/1 mL; ZINC SULFATE 2.5 mg/1 mL
INACTIVE INGREDIENTS: BENZALKONIUM CHLORIDE; BORIC ACID; EDETATE DISODIUM; WATER; SODIUM CHLORIDE; SODIUM CITRATE

Active ingredients Purpose

Tetrahydrozoline HCI 0.05.................Redness reliever

Zinc sulfate 0.25%...........................Astringent

Uses

- for temporary relief of discomfort and redness of the eye due to minor eye irritations

Warnings

For external use only

Ask a doctor before use if you have

narrow angle glaucoma.

When using this product

- pupils may become enlarged temporarily
- overuse may cause more eye redness
- remove contact lenses before using
- do not use if this solution changes color or becomes cloudy
- do not touch tip of container to any surface to avoid contamination
- replace cap after each use

Stop use and ask a doctor if

- you feel eye pain
- changes in vision occur
- redness or irritation of the eye lasts
- condition worsens or lasts more than 72 hours

PREGNANCY OR BREAST FEEDING

If pregnant or breast-feeding, ask a health professional before use.

Keep out of reach of children. If swallowed, get medical help or contact a Poison Control Center right away.

Directions

- to open bottle, push cap down and twist counter-clockwise. To close bottle, twist clockwise until it stops turning.
- put 1 to 2 drops in the affected eye(s) up to 4 times daily
- children under 6 years of age: ask a doctor

Other information

- some users may experience a brief tingling sensation
- store at 15° to 25°C (59° to °F)

Inactive ingredients

benzalkonium chloride, boric acid, edetate disodium, purified water, sodium chloride, sodium citrate

DOSAGE AND ADMINISTRATION

Distributed by:

Geiss, Destin & Dunn, Inc.

Peachtree City, GA 30269

www.valuelabels.com

1-866-696-0957

Made in Korea